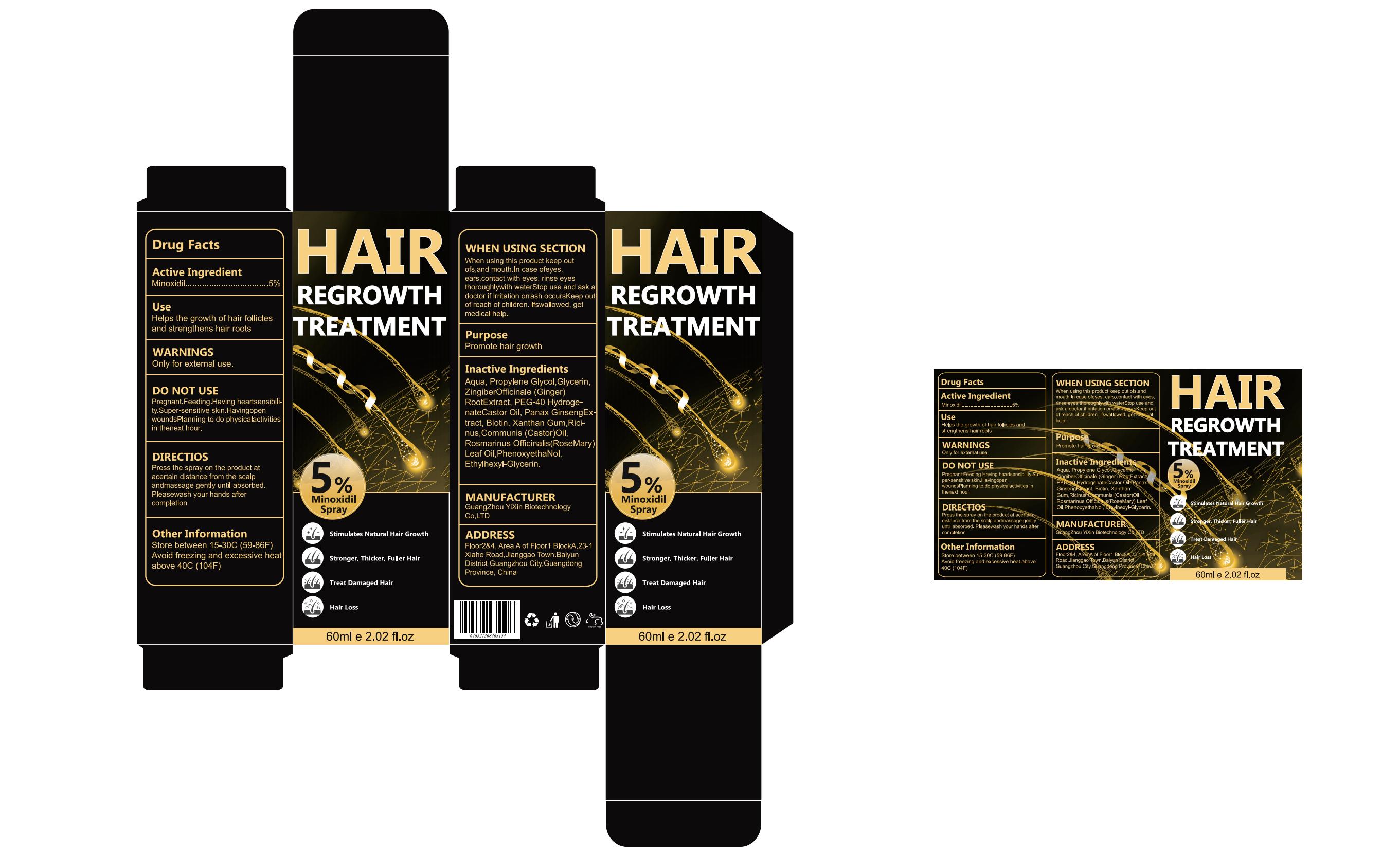 DRUG LABEL: HAIR REGROWTH IREATMENT
NDC: 83788-301 | Form: LIQUID
Manufacturer: Xiamen Panmai Technology Co., Ltd
Category: otc | Type: HUMAN OTC DRUG LABEL
Date: 20240516

ACTIVE INGREDIENTS: MINOXIDIL 5 g/100 mL
INACTIVE INGREDIENTS: PANAX NOTOGINSENG ROOT; RICINUS COMMUNIS LEAF; WATER; XANTHAN GUM; PROPYLENE GLYCOL; BIOTIN; GINGER; CASTOR OIL; GLYCERIN; ETHYLHEXYLGLYCERIN; ROSEMARY OIL; PHENOXYETHANOL; POLYOXYL 40 CASTOR OIL

83788-301

Active Ingredient

Minoxidil 5%

Purpose

HAIR REGROWTH

Use

Helps the growth of hair follicles
and strengthens hair roots

Warnings

Only for external use.

Do not use

Pregnant.Feeding.Having heartsensibilty. Super-sensitive skin. Havingopen woundsPlanning to do physicalactivities in thenext hour.

When Using

When using this product keep out ofs,and mouth.In case ofeyesears,contact with eyes, rinse eves thoroughlywith waterStop use and ask a doctor if irritation orrash occursKeep ol of reach of children. lfswallowed, get medical help.

Stop Use

Pregnant.Feeding.Having heartsensibilily.Super-sensitive skin.Havingopenwounds Planning to do physicalactivitiesin thenext hour.

Ask Doctor

use and ask adoctor if irritation orrash occurs Keep out of reach of children. lfswallowed, get medical help.

Keep Oot Of Reach Of Children

When using this product keep out ofs,and mouth.In case ofeyes ears,contact with eyes, rinse eves thoroughlywith waterStop use and ask doctor if irritation orrash occursKeep ol of reach of children. lfswallowed, get medical help.

Directions

Press the spray on the product at acertain distance from the scalp andmassage gently until absorbed. Pleasewash your hands after
completion

Other information

Store between 15-30C(59-86F) Avoid freezing and excessive heat above 40C(104F)

Inactive ingredients

Aqua, Propylene Glycol,Glycerin, ZingiberOfficinale (Ginger) RootExtract, PEG-40 HydrogenateCastor Oil, Panax GinsengExtract, Biotin, Xanthan Gum.Ricinus.Communis (Castor)Oil,Rosmarinus Officinalis(RoseMary) Leaf Oil,PhenoxyethaNol, Ethylhex-yl-Glycerin.